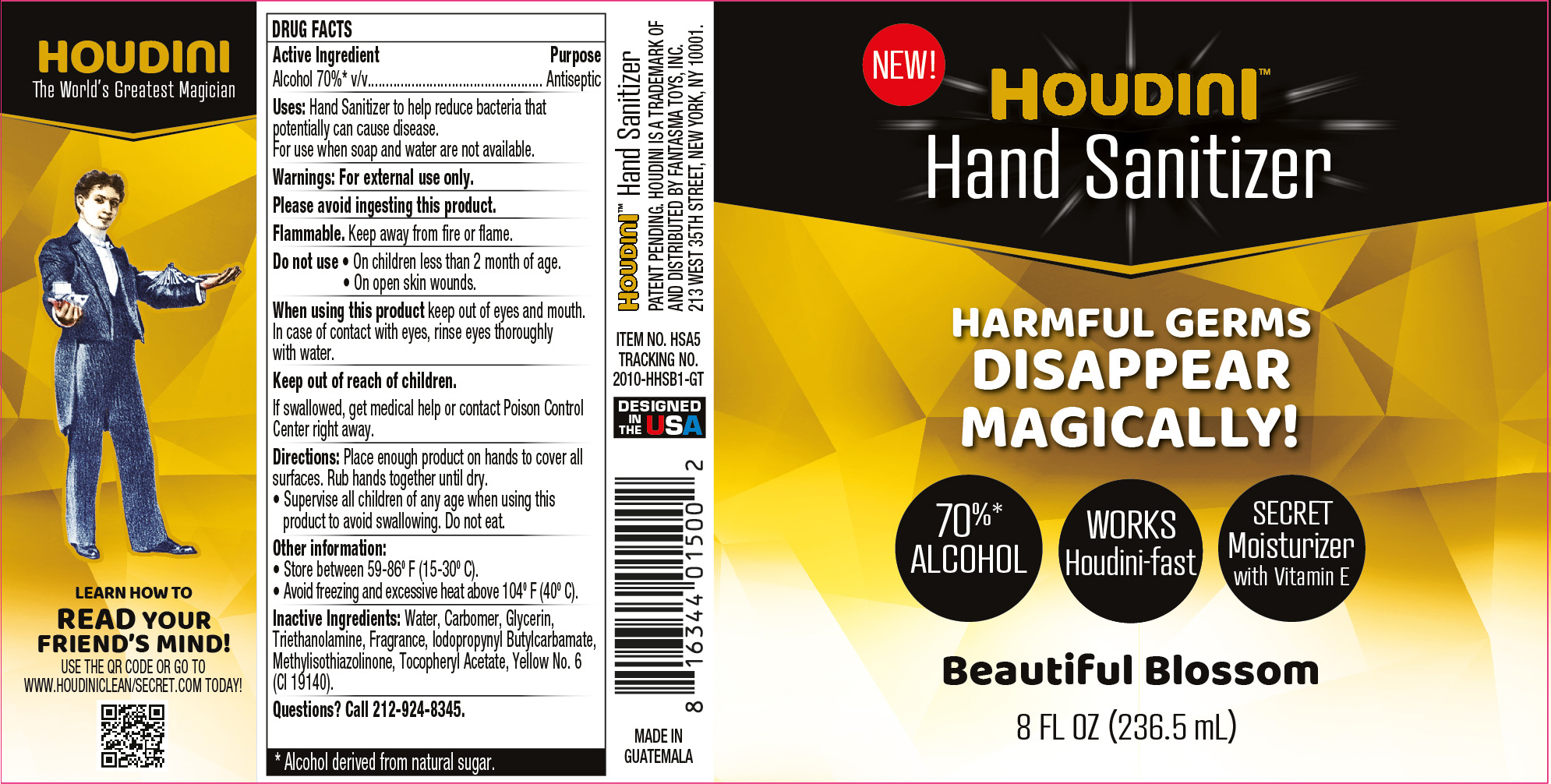 DRUG LABEL: Houdini Hand Sanitizer Beautiful Blossom
NDC: 79512-001 | Form: GEL
Manufacturer: Fantasma Toys
Category: otc | Type: HUMAN OTC DRUG LABEL
Date: 20200721

ACTIVE INGREDIENTS: ALCOHOL 70 mL/100 mL
INACTIVE INGREDIENTS: IODOPROPYNYL BUTYLCARBAMATE; FD&C YELLOW NO. 6; WATER; CARBOMER HOMOPOLYMER, UNSPECIFIED TYPE; GLYCERIN; METHYLISOTHIAZOLINONE; .ALPHA.-TOCOPHEROL ACETATE; TROLAMINE

Houdini Hand Sanitizer Beautiful Blossom

Active Ingredient

Alcohol 70%* v/v

*Alcohol derived from natural sugar

Purpose

Antiseptic

Uses

Hand Sanitizer to help reduce bacteria that potentially can cause disease.

For use when soap and water are not available.

Warnings

For external use only.

Please avoid ingesting this product.

Flammable. Keep away from fire or flame.

Do not use

- On children less than 2 months of age.
- On open skin wounds.

When using this product

keep out of eyes and mouth. In case of contact with eyes, rinse eyes thoroughly with water.

Keep out of reach of children.

If swallowed, get medical help or contact Poison Control Center right away.

Directions

Place enough product on hands to cover all surfaces. Rub hands together until dry.

- Supervise all children of any age when using this product to avoid swallowing. Do not eat.

Other information

- Store between 59-86F (15-30C)
- Avoid freezing and excessive heat above 104F (40C)

Inactive Ingredients

Water, Carbomer, Glycerin, Triethanolamine, Fragrance, Iodopropynyl Butylcarbamate, Methylisothiazolinone, Tocopheryl Acetate, Yellow No. 6 (CI 19140).

Questions?

Call 212-924-8345

Company Information

DISTRIBUTED BY FANTASMA TOYS, INC.

213 WEST 35TH STREET, NEW YORK, NY 10001

Product Packaging

HOUDINI

Hand Sanitizer

HARMFUL GERMS

DISAPPEAR MAGICALLY!

70% ALCOHOL

WORKS Houdini-fast

SECRET Moisturizer with Vitamin E

Beautiful Blossom

8 FL OZ (236.5 mL)